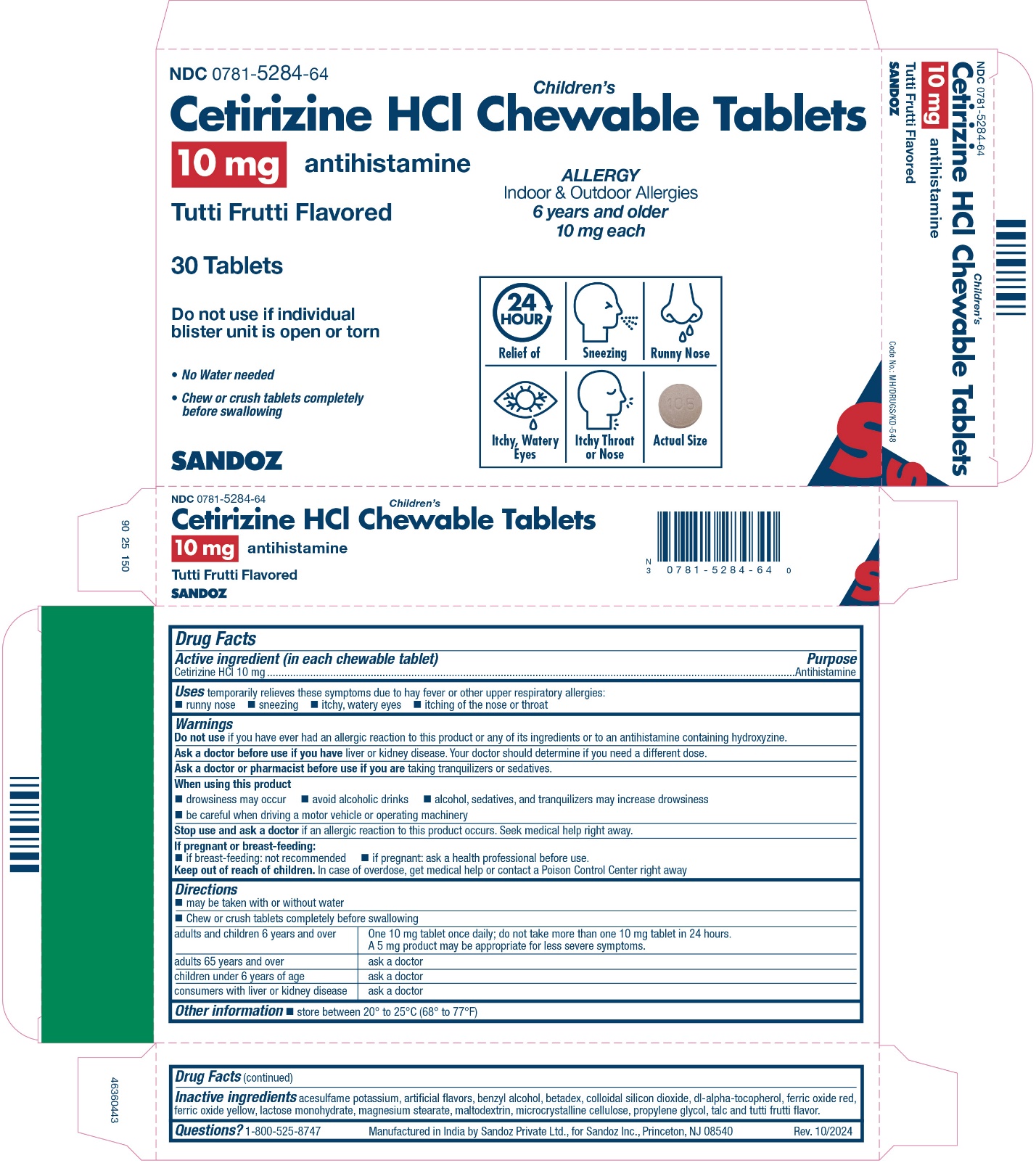 DRUG LABEL: Cetirizine Hydrochloride
NDC: 0781-5284 | Form: TABLET, CHEWABLE
Manufacturer: Sandoz Inc
Category: otc | Type: HUMAN OTC DRUG LABEL
Date: 20241009

ACTIVE INGREDIENTS: CETIRIZINE HYDROCHLORIDE 10 mg/1 1
INACTIVE INGREDIENTS: ACESULFAME POTASSIUM; BENZYL ALCOHOL; BETADEX; SILICON DIOXIDE; .ALPHA.-TOCOPHEROL ACETATE, DL-; FERRIC OXIDE RED; FERRIC OXIDE YELLOW; LACTOSE MONOHYDRATE; MAGNESIUM STEARATE; MALTODEXTRIN; MICROCRYSTALLINE CELLULOSE; PROPYLENE GLYCOL; TALC

Drug Facts

Active ingredient

(in each chewable tablet)

Cetirizine HCl 10 mg

Purpose

Antihistamine

Keep out of reach of children. In case of overdose, get medical help or contact a Poison Control Center right away.

Uses

Temporarily relieves these symptoms due to hay fever or other upper respiratory allergies:

- runny nose
- sneezing
- itchy, watery eyes
- itching of the nose or throat

Warnings

Do not use if you have ever had an allergic reactions to this product or any of its ingredients or to an antihistamine containing hydroxyzine.

Ask a doctor before use if you have liver or kidney disease. Your doctor should determine if you need a different dose.

Ask a doctor or pharmacist before use if you are taking tranquilizers or sedatives.

When using this product

- drowsiness may occur
- avoid alcoholic drinks
- alcohol, sedatives, and tranquilizers may increase drowsiness
- be careful when driving a motor vehicle or operating machinery

Stop use and ask a doctor if an allergic reaction to this product occurs. Seek medical help right away.

If pregnant or breast-feeding:

- if breast-feeding: not recommended
- if pregnant: ask a health professional before use.

Keep out of reach of children. In case of overdose, get medical help or contact a Poison Control Center right away.

Directions

- may be taken with or without water
- Chew or crush tablets completely before swallowing

adults and children 6 years and over | one 10 mg tablet once daily; do not take more than one 10 mg tablet in 24 hours. A 5 mg product may be appropriate for less severe symptoms.
adults 65 years and over | ask a doctor
children under 6 years of age | ask a doctor
consumers with liver or kidney disease | ask a doctor

Other information

- Store between 20º to 25º C (68º to 77º F)

Inactive ingredients

acesulfame potassium, artificial flavors, benzyl alcohol, betadex, colloidal silicon dioxide, dl-alpha-tocopherol, ferric oxide red, ferric oxide yellow, lactose monohydrate, magnesium stearate, maltodextrin, microcrystalline cellulose, propylene glycol, talc and tutti frutti flavor

Questions? 1-800-525-8747

Product of India

Manufactured by Sandoz Private Ltd.,

for Sandoz Inc., Princeton, NJ 08540

Rev.10/2024

Principal Display Panel

NDC 0781-5284-64

Children's

Cetirizine HCl Chewable Tablets

10 mg

antihistamine

Tutti Frutti Flavored

30 Tablets

Do not use if individual blister unit is open or torn

ALLERGY

Indoor & Outdoor Allergies

24 hour Relief of

- Sneezing
- Runny Nose
- Itchy, Watery Eyes
- Itchy Throat or Nose
No Water needed
Chew or crush tablets completely before swallowing

6 yrs. and older 10 mg each